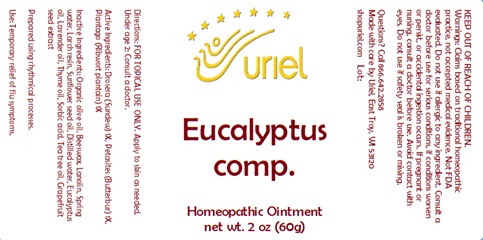 DRUG LABEL: Eucalyptus comp.
NDC: 48951-4194 | Form: OINTMENT
Manufacturer: Uriel Pharmacy Inc.
Category: homeopathic | Type: HUMAN OTC DRUG LABEL
Date: 20241211

ACTIVE INGREDIENTS: DROSERA ROTUNDIFOLIA 1 [hp_X]/1 g; PETASITES HYBRIDUS ROOT 1 [hp_X]/1 g; PLANTAGO MAJOR LEAF 1 [hp_X]/1 g
INACTIVE INGREDIENTS: YELLOW WAX; LANOLIN; WATER; LARIX DECIDUA RESIN; SUNFLOWER OIL; EUCALYPTUS OIL; LAVENDER OIL; THYME OIL; SORBIC ACID; CITRUS PARADISI SEED; OLIVE OIL; TEA TREE OIL

Eucalyptus comp.

INDICATIONS AND USAGE

Directions: FOR TOPICAL USE ONLY.

DOSAGE AND ADMINISTRATION

Apply to skin as needed. Under age 2: Consult a doctor.

ACTIVE INGREDIENT

Active Ingredients: Drosera (Sundew) 1X, Petasites (Butterbur) 1X, Plantago (Ribwort plantain) 1X

INACTIVE INGREDIENT

Inactive Ingredients: Organic olive oil, Beeswax, Lanolin, Spring water, Larch resin, Sunflower seed oil, Distilled water, Eucalyptus oil, Lavender oil, Thyme oil, Sorbic acid, Tea tree oil, Grapefruit seed extract

Prepared using rhythmical processes.

PURPOSE

Use: Temporary relief of flu symptoms.

KEEP OUT OF REACH OF CHILDREN.

Warnings: FOR EXTERNAL USE ONLY.
Claims based on traditional homeopathic practice, not accepted medical evidence. Not FDA evaluated. Do not use if allergic to any ingredient. Consult a doctor before use for serious conditions, if conditions worsen or persist, or accidental ingestion occurs. If pregnant or nursing, consult a doctor before use. Avoid contact with eyes. Do not use if safety seal is broken or missing.

Questions? Call 866.642.2858

Made with care by Uriel, East Troy, WI 53120

shopuriel.com Lot: